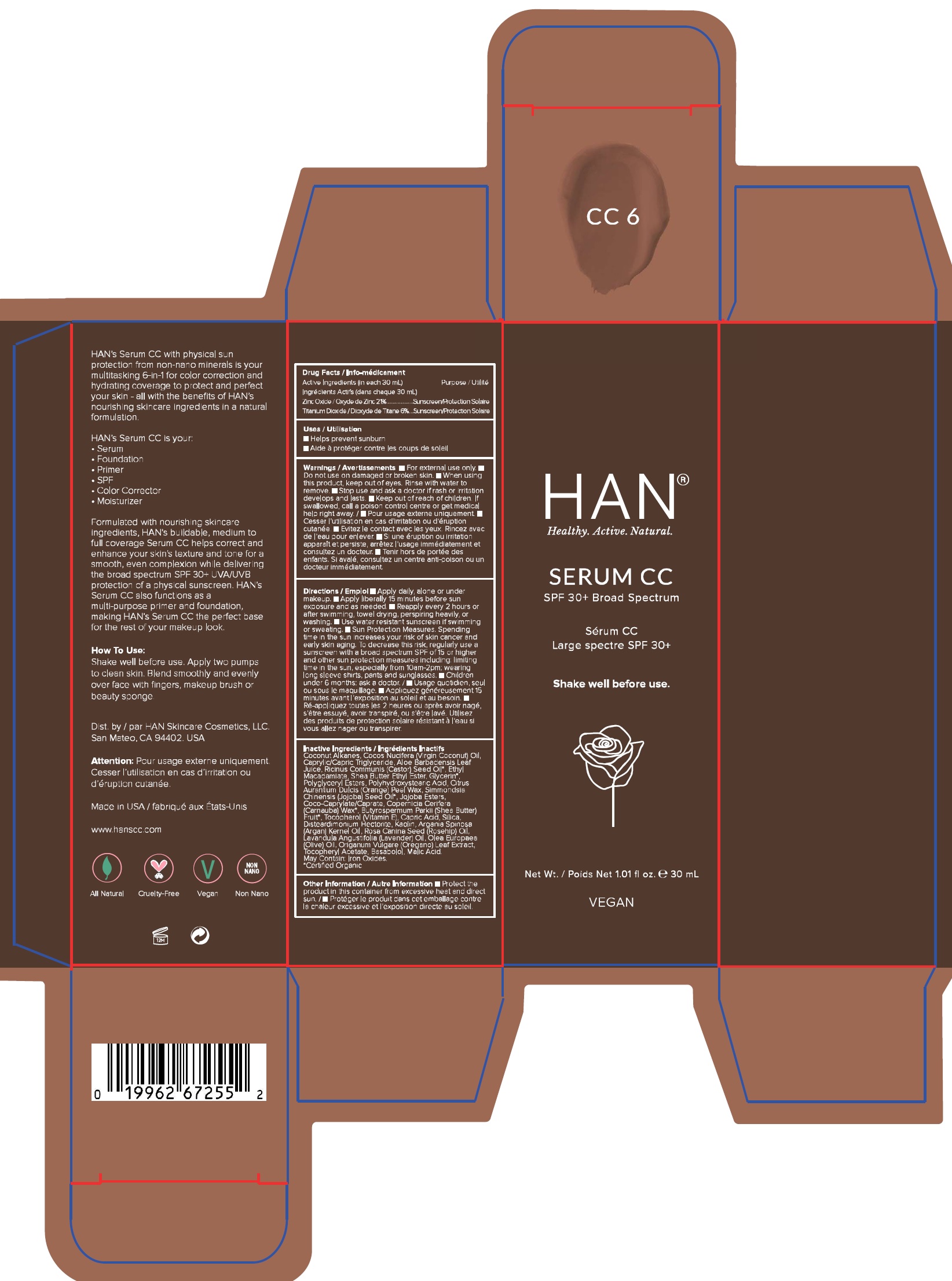 DRUG LABEL: CC Cream SPF 30
NDC: 79489-0010 | Form: CREAM
Manufacturer: HAN Skin Care Cosmetics, LLC
Category: otc | Type: HUMAN OTC DRUG LABEL
Date: 20211026

ACTIVE INGREDIENTS: ZINC OXIDE 210 mg/1 mL; TITANIUM DIOXIDE 60 mg/1 mL
INACTIVE INGREDIENTS: COCONUT ALKANES; COCONUT OIL; TRICAPRILIN; ALOE VERA LEAF; CASTOR OIL; ETHYL MACADAMIATE; GLYCERIN; ORANGE PEEL WAX; JOJOBA OIL; COCOYL CAPRYLOCAPRATE; CARNAUBA WAX; SHEA BUTTER; TOCOPHEROL; CAPRIC ACID; SILICON DIOXIDE; DISTEARDIMONIUM HECTORITE; KAOLIN; ARGAN OIL; ROSA MOSCHATA OIL; LAVENDER OIL; OLIVE OIL; OREGANO; .ALPHA.-TOCOPHEROL ACETATE; LEVOMENOL; MALIC ACID; FERRIC OXIDE RED

CC Cream SPF 30

Active Ingredients(in each 30 ml)

Zinc Oxide 21%

Titanium Dioxide 6%

Purpose

Sunscreen

Uses

- Helps prevent sunburn

warnings

- For external use only.

Do not use

- on damaged or broken skin.

When using this product,

- Keep out of eyes. Rinse with water to remove.

Stop use and ask a doctor

- if rash or irritation develops and lasts.

Keep out of reach of children.

If swallowed, call a poison control center or get medical help right away.

Directions

- Apply daily, alone or under makeup.
- Apply liberally 15 minutes before sun exposure and as needed.
- Reapply every 2 hours or after swimming, towel drying, perspiring heavily, or washing.
- Use water resistant sunscreen if swimming or sweating.
- Sun Protecion Measures. Spending time in the sun increases your risk of skin cancer and early skin aging. To decrease this risk, regularly use a sunscreen with a broad spectum SPF of 15 or higher and other sun protection measure including: limiting time in the sun, especially from 10am-2pm; wearing long sleeve shirts, pants and sunglasses.
- Children under 6 months: ask a doctor.

Inactive Ingredients

Coconut Alkanes, Cocos Nucifera (Virgin Coconut) Oil, Caprylic/Capric Triglyceride, Aloe Barbadensis Leaf Juice, Ricinus Communis (Castor) Seed Oil*, Ethyl Macadamiate, Shea Butter Ethyl Ester, Glycerin*, Polyglyceryl Esters, Polyhydroxystearic Acid, Citrus Aurantium Dulcis (Orange) Peel Wax, Simmondsia Chinensis (Jojoba) Seed Oil*, Jojoba Esters, Coco-Caprylate/Caprate, Copernicia Cerifera (Carnauba) Wax*, Butyrospermum Parkii (Shea Butter) Fruit*, Tocopherol (Vitamin E), Capric Acid, Silica, Disteardimonium Hectorite, Kaolin, Argania Spinosa (Argan) Kernel Oil, Rosa Canina Seed (Rosehip) Oil, Lavandula Angustifolia (Lavender) Oil, Olea Europaea (Olive) Oil, Origanum Vulgare (Oregano) Leaf Extract,
Tocopheryl Acetate, Basabolol, Malic Acid. May Contain: Iron Oxides.
*Certified Organic

Other Information

- Protect the product in this container from excessive heat and direct sun.